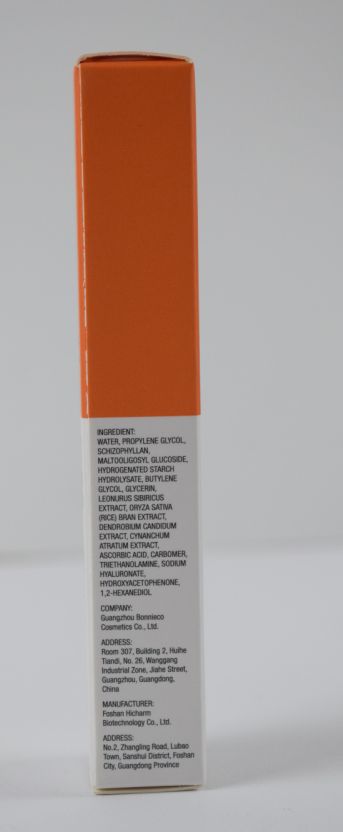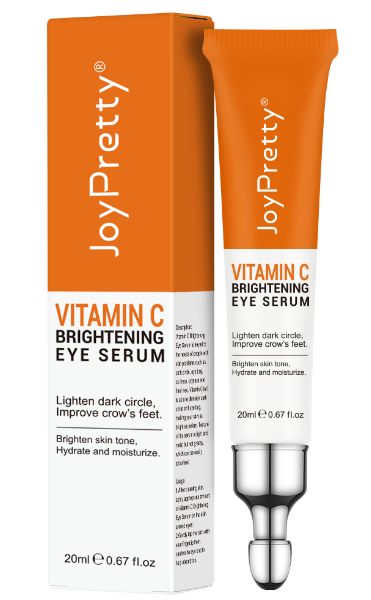 DRUG LABEL: JoyPretty VITAMIN C BRIGHTENING EYE SERUM
NDC: 83675-031 | Form: CREAM
Manufacturer: Guangzhou Hanhai Trading Co., Ltd
Category: otc | Type: HUMAN OTC DRUG LABEL
Date: 20231210

ACTIVE INGREDIENTS: MALTOOLIGOSYL GLUCOSIDE 3.2 g/100 mL; BUTYLENE GLYCOL 2.68 g/100 mL; GLYCERIN 2.5 g/100 mL; DENDROBIUM MONILIFORME WHOLE 1.92 g/100 mL; VINCETOXICUM ATRATUM STEM 1.56 g/100 mL; SIZOFIRAN 3.2 g/100 mL; ASCORBIC ACID 1.5 g/100 mL; HYALURONATE SODIUM 0.1 g/100 mL; LEONURUS SIBIRICUS LEAF 2 g/100 mL; PROPYLENE GLYCOL 5 g/100 mL; HYDROGENATED STARCH HYDROLYSATE 3.15 g/100 mL; RICE BRAN 2 g/100 mL
INACTIVE INGREDIENTS: CARBOMER HOMOPOLYMER, UNSPECIFIED TYPE; TROLAMINE; 1,2-HEXANEDIOL; WATER; HYDROXYACETOPHENONE

Active Ingredient

PROPYLENE GLYCOL, SCHIZOPHYLLAN, MALTOOLIGOSYL GLUCOSIDE, HYDROGENATED STARCH HYDROLYSATE, BUTYLENE GLYCOL, GLYCERIN, LEONURUS SIBIRICUS EXTRACT, ORYZA SATIVA (RICE) BRAN EXTRACT, DENDROBIUM CANDIDUM EXTRACT, CYNANCHUM ATRATUM EXTRACT, ASCORBIC ACID, SODIUM HYALURONATE

Purpose

Lighten dark circle,lmprove crow's feet.
Brighten skin tone, Hydrate and moisturize.

Use

1.After cleaning skin,
apply appropriate amount of Vitamin C Brightening Eye Serum on the skin around eyes;
2.Gently tap the skin with your fingertip from
canthus to eye end to help absorption.

Warnings

CAUTIONS:
For external use only. Keep out of reach of children. Avoid contact with eyes. Discontinue use if signs of irritation or rash occur. Store in a cool and dry place.

Do not use

If discomfort arises, please immediately stop using the product and seek the assistance of a dermatologist.

When Using

In case of sensitive skin, please test the product on the inside of the arm first.
In case of contact with the eyes, rinse immediately with plenty of water.

Stop Use

If discomfort arises, please immediately stop using the product and seek the assistance of a dermatologist.

Ask Doctor

If discomfort arises, please immediately stop using the product and seek the assistance of a dermatologist.

Keep Oot Of Reach Of Children

Directions

1.After cleaning skin,
apply appropriate amount of Vitamin C Brightening Eye Serum on the skin around eyes;
2.Gently tap the skin with your fingertip from
canthus to eye end to help absorption.

Inactive ingredients

WATER, CARBOMER, TRIETHANOLAMINE, HYDROXYACETOPHENONE, 1,2-HEXANEDIOL